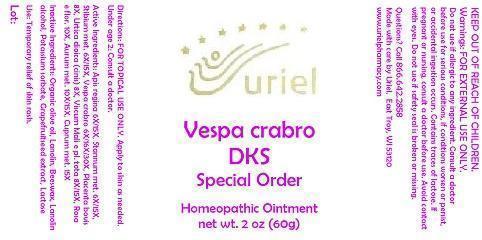 DRUG LABEL: Vespa crabro DKS Special Order
NDC: 48951-9239 | Form: OINTMENT
Manufacturer: Uriel Pharmacy Inc.
Category: homeopathic | Type: HUMAN OTC DRUG LABEL
Date: 20150227

ACTIVE INGREDIENTS: ROYAL JELLY 6 [hp_X]/1 g; TIN 6 [hp_X]/1 g; ANTIMONY 6 [hp_X]/1 g; VESPA CRABRO 6 [hp_X]/1 g; BOS TAURUS PLACENTA 8 [hp_X]/1 g; URTICA DIOICA 8 [hp_X]/1 g; EQUISETUM ARVENSE TOP 8 [hp_X]/1 g; VISCUM ALBUM FRUITING TOP 8 [hp_X]/1 g; SEDUM ROSEUM WHOLE 10 [hp_X]/1 g; GOLD 10 [hp_X]/1 g; COPPER 15 [hp_X]/1 g
INACTIVE INGREDIENTS: OLIVE OIL; LANOLIN; YELLOW WAX; LANOLIN ALCOHOLS; POTASSIUM SORBATE; CITRUS PARADISI SEED; LACTOSE

Vespa crabro DKS Special Order

INDICATIONS AND USAGE

Directions: FOR TOPICAL USE ONLY.

DOSAGE AND ADMINISTRATION

Apply to skin as needed. Under age 2: Consult a doctor.

ACTIVE INGREDIENT

Active Ingredients: Apis regina 6X/15X, Stannum met. 6X/15X, Stibium met. 6X/15X, Vespa crabro 6X/16X/30X, Placenta bovis 8X, Urtica dioica (cinis) 8X, Viscum Mali e pl. tota 8X/15X, Rosa e flor. 10X, Aurum met. 10X/15X, Cuprum met. 15X

INACTIVE INGREDIENT

Inactive Ingredients: Organic olive oil, Lanolin, Beeswax, Lanolin alcohol, Potassium sorbate, Grapefruitseed extract, Lactose

PURPOSE

Use: Temporary relief of skin rash.

KEEP OUT OF REACH OF CHILDREN.

Warnings: FOR EXTERNAL USE ONLY.
Do not use if allergic to any ingredient. Consult a doctor before use for serious conditions, if conditions worsen or persist, or accidental ingestion occurs. Contains traces of lactose. If pregnant or nursing, consult a doctor before use. Avoid contact with eyes. Do not use if safety seal is broken or missing.

QUESTIONS

Questions? Call 866.642.2858 Made with care by Uriel, East Troy, WI 53120 www.urielpharmacy.com